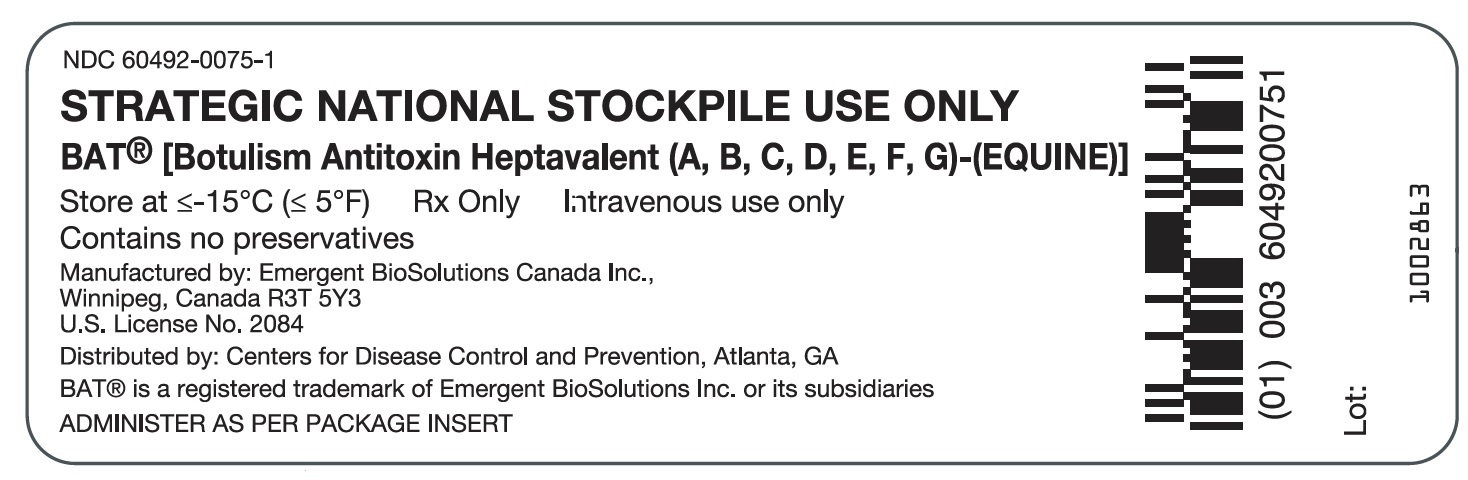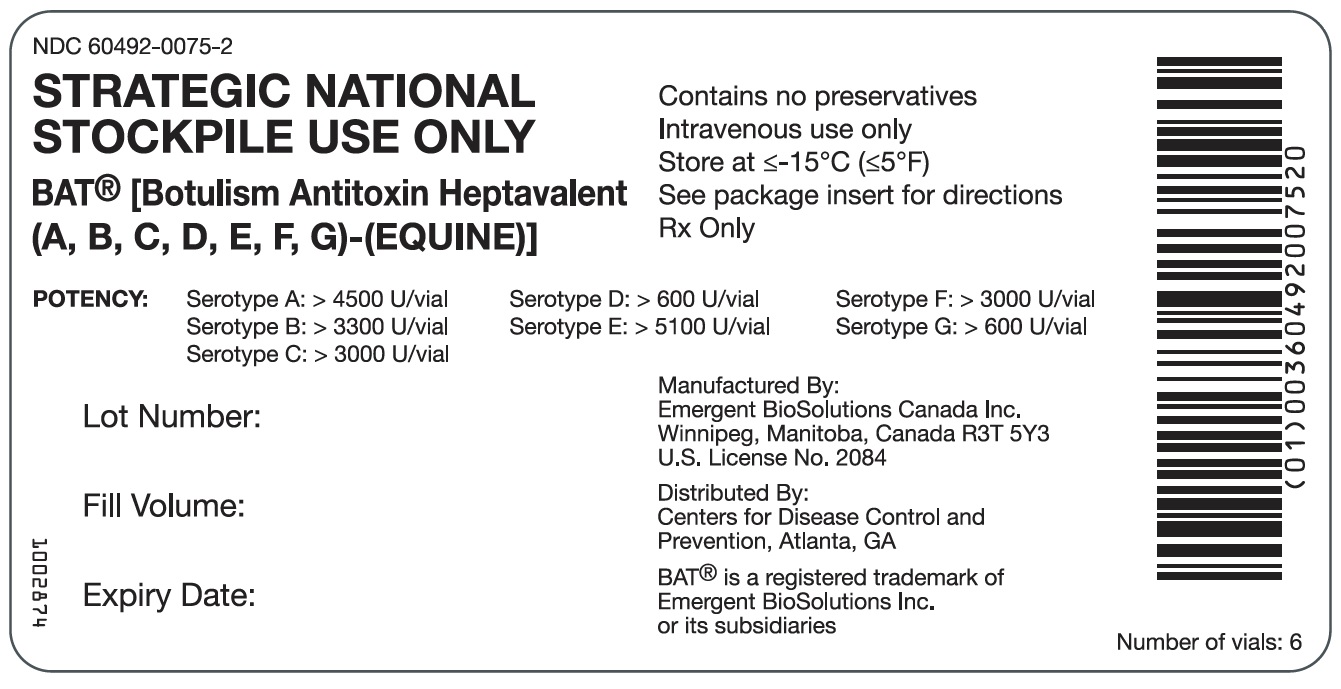 DRUG LABEL: BAT
NDC: 60492-0075 | Form: LIQUID
Manufacturer: Emergent BioSolutions Canada Inc
Category: other | Type: PLASMA DERIVATIVE
Date: 20250515

ACTIVE INGREDIENTS: EQUINE BOTULINUM NEUROTOXIN A IMMUNE FAB2 4500 [iU]/10 mL; EQUINE BOTULINUM NEUROTOXIN B IMMUNE FAB2 3300 [iU]/10 mL; EQUINE BOTULINUM NEUROTOXIN C IMMUNE FAB2 3000 [iU]/10 mL; EQUINE BOTULINUM NEUROTOXIN D IMMUNE FAB2 600 [iU]/10 mL; EQUINE BOTULINUM NEUROTOXIN E IMMUNE FAB2 5100 [iU]/10 mL; EQUINE BOTULINUM NEUROTOXIN F IMMUNE FAB2 3000 [iU]/10 mL; EQUINE BOTULINUM NEUROTOXIN G IMMUNE FAB2 600 [iU]/10 mL
INACTIVE INGREDIENTS: POLYSORBATE 80; MALTOSE MONOHYDRATE

HIGHLIGHTS OF PRESCRIBING INFORMATION

These highlights do not include all the information needed to use BAT® safely and effectively. See full prescribing information for BAT®.
BAT® [Botulism Antitoxin Heptavalent (A, B, C, D, E, F, G) - (Equine)]
Sterile Solution for Injection
Initial U.S. Approval: 2013

1 INDICATIONS AND USAGE

BAT [Botulism Antitoxin Heptavalent (A, B, C, D, E, F, G) – (Equine)] is a mixture of immune globulin fragments indicated for the treatment of symptomatic botulism following documented or suspected exposure to botulinum neurotoxin serotypes A, B, C, D, E, F, or G in adults and pediatric patients.

The effectiveness of BAT is based solely on efficacy studies conducted in animal models of botulism. (1)

2 DOSAGE AND ADMINISTRATION

For intravenous use only.

Administer BAT by slow intravenous infusion after dilution 1:10 in normal saline at the dose recommended in the following table. (2)

Patient Group | Dose | Starting Infusion Rate; (first 30 minutes) | Incremental Infusion Rate if Tolerated; (every 30 minutes) | Maximum Infusion Rate
Adults; (≥ 17 years) | One vial | 0.5 mL/min | Double the rate | 2 mL/min
Pediatric; (1 year to <17 years) | 20 – 100% of adult dose | 0.01 mL/kg/min; Do not exceed the adult rate | 0.01 mL/kg/min | 0.03 mL/kg/min; Do not exceed the adult rate
Infants; (< 1 year) | 10% of adult dose regardless of body weight | 0.01 mL/kg/min | 0.01 mL/kg/min | 0.03 mL/kg/min

3 DOSAGE FORMS AND STRENGTHS

Each single-use vial contains a minimum potency of: (3)

- 4,500 Units (U) for serotype A antitoxin,
- 3,300 U for serotype B antitoxin,
- 3,000 U for serotype C antitoxin,
- 600 U for serotype D antitoxin,
- 5,100 U for serotype E antitoxin,
- 3,000 U for serotype F antitoxin, and
- 600 U for serotype G antitoxin

4 CONTRAINDICATIONS

None. (4)

5 WARNINGS AND PRECAUTIONS

- Hypersensitivity reactions including anaphylaxis. Prepare for monitoring and management of allergic reactions (5.1).
- Delayed allergic reactions (serum sickness). Patient monitoring is recommended (5.2).
- Infusion reactions. Monitor and slow or interrupt infusion and administer treatment based on the severity of the reaction (5.3).
- Interference with non-glucose specific blood sugar testing systems. Use glucose-specific testing systems (5.4).
- BAT is made from equine plasma and may contain infectious agents e.g. viruses (5.5).

6 ADVERSE REACTIONS

- The most common adverse reactions observed in ≥5% of healthy volunteers in clinical trials were headache, nausea, pruritus, and urticaria (6.1).
- The most common adverse reactions reported in ≥1% of patients in a clinical study were pyrexia, rash, chills, nausea, and edema (6.1).
- One serious adverse reaction of hemodynamic instability was observed in one patient in the clinical study (6.1).

To report SUSPECTED ADVERSE REACTIONS, contact Emergent BioSolutions Canada Inc. at 1-800-768-2304 or FDA at 1-800-FDA-1088 or www.fda.gov/medwatch.

8 USE IN SPECIFIC POPULATIONS

- Pediatric: Limited safety data is available in the pediatric population.
  Dosing in pediatric patients is based on Salisbury Rule (8.4).

FULL PRESCRIBING INFORMATION

1 INDICATIONS AND USAGE

BAT [Botulism Antitoxin Heptavalent (A, B, C, D, E, F, G) – (Equine)] is a mixture of immune globulin fragments indicated for the treatment of symptomatic botulism following documented or suspected exposure to botulinum neurotoxin serotypes A, B, C, D, E, F, or G in adults and pediatric patients.

The effectiveness of BAT is based on efficacy studies conducted in animal models of botulism.

2 DOSAGE AND ADMINISTRATION

BAT is for intravenous use only.

2.1 Dosage and Administration

- Each vial of BAT contains a minimum potency for serotypes A, B, C, D, E, F, and G antitoxin [see Dosage Forms and Strengths (3)].
- For adult, pediatric, and infant patient groups, administer a dose of BAT according to Table 1. For details on pediatric dosing by body weight see Table 2.
- Administer all BAT doses after dilution 1:10 in normal saline by slow intravenous infusion according to the varying infusion rates in Table 1.
- Monitor vital signs throughout the infusion. If tolerated, the infusion rate can be increased incrementally up to the maximum infusion rate, and continued for the remainder of the administration. Decrease infusion rate if the patient develops discomfort or infusion-related adverse reactions.

Table 1 BAT Dosing Guide and Intravenous Infusion Rate
Patient Group | Dose | Starting Infusion Rate; (first 30 minutes) | Incremental Infusion Rate if Tolerated; (every 30 minutes) | Maximum Infusion Rate
Adults; (≥ 17 years) | One vial | 0.5 mL/min | Double the rate | 2 mL/min
Pediatric; (1 year to < 17 years) | 20 – 100% of adult dose | 0.01 mL/kg/min; Do not exceed the adult rate. | 0.01 mL/kg/min | 0.03 mL/kg/min; Do not exceed the adult rate
Infants; (< 1 year) | 10% of adult dose regardless of body weight | 0.01 mL/kg/min | 0.01 mL/kg/min | 0.03 mL/kg/min

Calculate pediatric BAT dose by body weight according to Table 2.

Table 2 Pediatric Dosing Guide for BAT Based on Salisbury Rule (1 Year to < 17 Years)
Body Weight; (kg) | Percent of Adult Dose*; (%)
10-14 | 20**
15-19 | 30
20-24 | 40
25-29 | 50
30-34 | 60
35-39 | 65
40-44 | 70
45-49 | 75
50-54 | 80
≥ 55 | 100
*Dosing guide is based on the Salisbury Rule:
• Body weight ≤ 30 kg: 2x weight (kg) = % adult dose to administer
• Body weight > 30 kg: weight (kg) + 30 = % adult dose to administer
Do not exceed 1 vial dose regardless of body weight.
** Minimum pediatric dose is 20% of adult dose. See Table 1 for infant dose.

2.2 Preparation

1. Bring vial to room temperature.
  1. If frozen, thaw vial by placing in a refrigerator at 36 to 46 °F (2 to 8 °C) until the contents are thawed for approximately 14 hours.
  2. Product can be thawed rapidly by placing at room temperature for one hour followed by a water bath at 98.6 °F (37 °C) until thawed.
  3. Do not thaw this product in a microwave oven. Do not refreeze the vial.
2. Inspect vial to ensure there is no damage to the seal or vial. If damaged, discard the vial.
3. Do not shake the vial during preparation to avoid foaming.
4. Dilute 1:10 in 0.9% Sodium Chloride Injection, USP (saline) by adding BAT solution from the vial to the appropriate amount of saline in an IV bag. Do not use any other diluents. As the fill volume per vial varies by lot number (ranging from 10 to 26 milliliters per vial), 90 to 235 milliliters of saline will be required. Withdraw the entire contents of the vial to obtain the total volume in the vial. If a partial vial is required (for pediatric dosing), the entire content of the vial should be withdrawn to ensure accurate calculation of the dosage [Table 2].
5. Visually inspect the product for particulate matter and discoloration prior to administration. Do not use if the solution is turbid, cloudy, or contains particles other than a few translucent-to-white proteinaceous particulates.
6. Use an intravenous line with constant infusion pump. Use a 15-micron sterile, non-pyrogenic, low protein binding in-line filter.
7. BAT vials are for single use only and contain no preservative. Once punctured, use the vial contents to prepare the infusion bag and administer as soon as possible.
8. Discard any unused portion.

3 DOSAGE FORMS AND STRENGTHS

BAT is a sterile solution of purified F(ab')2 plus F(ab')2-related immune globulin fragments derived from equine plasma, containing antitoxin activity to botulinum neurotoxins A, B, C, D, E, F, and G.

Each single-use vial, regardless of size or fill volume, contains a minimum antitoxin potency of:

- 4,500 U serotype A antitoxin,
- 3,300 U serotype B antitoxin,
- 3,000 U serotype C antitoxin,
- 600 U serotype D antitoxin,
- 5,100 U serotype E antitoxin,
- 3,000 U serotype F antitoxin, and
- 600 U serotype G antitoxin.

4 CONTRAINDICATIONS

None.

5 WARNINGS AND PRECAUTIONS

5.1 Hypersensitivity Reactions

Severe hypersensitivity reactions, including anaphylactic and anaphylactoid reactions may occur following BAT administration. Patients who have had previous therapy with an equine-derived antivenom/antitoxin, with a history of hypersensitivity to horses, asthma, or hay fever are at a greater risk for developing severe hypersensitivity reactions to BAT. Administer BAT in a setting with appropriate equipment, medication, including epinephrine, and personnel trained in the management of hypersensitivity, anaphylaxis, and shock.

Monitor all patients for signs and symptoms of acute allergic reaction (e.g. urticaria, pruritus, erythema, angioedema, bronchospasm with wheezing or cough, stridor, laryngeal edema, hypotension, tachycardia) during and following the BAT infusion. In case of hypersensitivity reaction, discontinue BAT administration immediately and administer appropriate emergency care. Have immediately available medications such as epinephrine for emergency treatment of acute hypersensitivity reactions.

For patients at risk for hypersensitivity reaction, begin BAT administration at the lowest rate achievable (< 0.01 mL/min) and monitor.

5.2 Delayed Allergic Reactions (Serum Sickness)

Delayed allergic reactions (serum sickness e.g. fever, urticarial or maculopapular rash, myalgia, arthralgia, and lymphadenopathy) may occur following BAT administration, typically 10-21 days after infusion. Monitor patients for signs and symptoms of delayed allergic reaction.

If a delayed allergic reaction (serum sickness) is suspected, administer appropriate medical care.

5.3 Infusion Reactions

Chills, fever, headaches, nausea, and vomiting can be related to the rate of infusion. Arthralgia, myalgia and fatigue or vasovagal reactions may also develop. Carefully observe patients for the onset of these infusion reactions throughout the infusion period and immediately following an infusion.

Reduce the rate of infusion if the patient experiences infusion reactions and administer symptomatic therapy. If symptoms worsen, discontinue the infusion and administer appropriate medical care.

5.4 Interference with Blood Glucose Testing

The maltose contained in BAT can interfere with some types of blood glucose monitoring systems i.e. those based on glucose dehydrogenase pyrroloquinoline-quinone (GDH-PQQ) method. This can result in falsely elevated glucose readings and inappropriate administration of insulin, resulting in life-threatening hypoglycemia. Cases of true hypoglycemia may go untreated if the hypoglycemic state is masked by falsely elevated results [see Drug Interactions (7)].

5.5 Transmissible Infectious Agents

Because BAT is made from equine plasma, it may carry the risk of transmitting infectious agents e.g. viruses. The equine plasma pools are screened for the presence of certain infectious agents and the manufacturing process for BAT includes measures to inactivate and remove certain viruses [see Description (11)]. Despite these measures, such products can still potentially transmit disease. No cases of transmission of viral diseases have been associated with the use of BAT.

Report all infections thought by a physician to have been transmitted by BAT to Emergent BioSolutions Canada Inc. at 1-800-768-2304. Discuss the risks and benefits of this product with the patient or their legal guardian before administering it to the patient [see Patient Counseling Information (17)].

6 ADVERSE REACTIONS

The most common adverse reactions observed in ≥ 5 % of healthy volunteers in clinical trials were headache, nausea, pruritus, and urticaria.

The most common adverse reactions reported in ≥ 1% of patients in a clinical study were pyrexia, rash, chills, nausea and edema.

The following serious adverse reactions are discussed in detail in other sections of the labeling:

- Hypersensitivity reactions [see Warnings and Precautions (5.1)]
- Delayed allergic reactions/serum sickness [see Warnings and Precautions (5.2)]
- Infusion reactions [see Warnings and Precautions (5.3)]

6.1 Clinical Trials Experience

Because clinical trials are conducted under widely varying conditions, adverse reaction rates observed in the clinical trials of a drug cannot be directly compared to rates in the clinical trials of another drug and may not reflect the rates observed in practice.

In a randomized, double-blind, parallel arm trial conducted to evaluate the safety of BAT in healthy subjects, and to establish the pharmacokinetic profile of the seven botulinum antitoxin serotypes contained in BAT following intravenous (IV) administration, 40 subjects were randomized to receive either one (n=20) or two vials (n=20) of BAT.

In a second parallel arm, randomized, double-blind pharmacodynamic trial, 26 healthy subjects were randomized to receive either BAT in saline (n=16) or placebo (0.9% saline; n=10).

The most common adverse reactions in all healthy subjects were headache (9%), pruritus (5%), nausea (5%), and urticaria (5%). Other adverse reactions reported in less than 4% of subjects included pyrexia and throat discomfort. All reported adverse reactions were considered mild or moderate. No serious adverse reactions were reported. Two moderate acute allergic reactions that required premature termination of the infusion and treatment were reported. Reactions were predefined as mild if the subject was aware but could tolerate. Moderate reactions were predefined as discomfort enough to interfere with normal daily activity.

A total of 231 subjects with suspected or confirmed botulism were exposed to BAT in an open-label observational expanded access clinical study sponsored by the Centers for Disease Control and Prevention (CDC).

The majority of adult (213/216) and pediatric (13/15) subjects received one dose of BAT. Three adult subjects were exposed to a second dose of BAT, and two pediatric subjects each received two infant doses (10% of the adult dose). The administration of a second dose varied from seven hours to one month after the first dose.

Safety data was actively collected from treating physicians by the CDC. However, no on-site safety monitoring was performed, and the CDC relied on follow-up information provided by the treating physicians to determine the reporting frequencies for adverse reactions. Of the 231 subjects receiving BAT, safety information was available for 228 subjects. Adverse reactions were reported in 10% of all subjects. The most common adverse reactions were pyrexia (4%), rash (2%), chills (1%), nausea (1%), and edema (1%). Other adverse reactions were reported in less than 1% of subjects. No subject experienced anaphylaxis. One subject experienced a serious adverse reaction of hemodynamic instability characterized by bradycardia, tachycardia, and asystole during BAT administration. One subject experienced mild serum sickness (< 1%) with myalgia, arthralgia, and dark urine twelve days after BAT administration.

Table 3 Summary of Adverse Drug Reactions (ADR) Reported in Subjects that Received BAT through the CDC Expanded Access Clinical Study
System Organ Class | Preferred Term | Overall (N=228)
System Organ Class | Preferred Term | No. of Events | No. of Subjects | % of Subjects
ALL BODY SYSTEM | OVERALL | 37 | 23 | 10.1
Cardiac disorders | Cardiac arrest | 1 | 1 | 0.4
Cardiac disorders | Bradycardia | 1 | 1 | 0.4
Cardiac disorders | Tachycardia | 1 | 1 | 0.4
Gastrointestinal disorders | Vomiting | 1 | 1 | 0.4
Gastrointestinal disorders | Nausea | 2 | 2 | 0.9
General disorders and administration site conditions | Pyrexia | 9 | 9 | 3.9
General disorders and administration site conditions | Chest discomfort | 1 | 1 | 0.4
General disorders and administration site conditions | Edema | 2 | 2 | 0.9
General disorders and administration site conditions | Chills | 3 | 3 | 1.3
General disorders and administration site conditions | Feeling jittery | 1 | 1 | 0.4
Immune system disorders | Serum Sickness | 1 | 1 | 0.4
Investigations | Blood pressure increased | 1 | 1 | 0.4
Investigations | White blood cell count increased | 1 | 1 | 0.4
Psychiatric disorders | Agitation | 1 | 1 | 0.4
Psychiatric disorders | Anxiety | 1 | 1 | 0.4
Renal and urinary disorders | Urinary retention | 1 | 1 | 0.4
Respiratory, thoracic and mediastinal disorders | Bronchospasm | 1 | 1 | 0.4
Skin and subcutaneous tissue disorders | Erythema | 1 | 1 | 0.4
Skin and subcutaneous tissue disorders | Hyperhidrosis | 1 | 1 | 0.4
Skin and subcutaneous tissue disorders | Rash | 4 | 4 | 1.8
Vascular disorders | Hemodynamic instability | 1 | 1 | 0.4
Vascular disorders | Hypotension | 1 | 1 | 0.4
All adverse reactions were classified according to MedDRA Version 15.0 and are ranked according to medical significance within a given SOC.

6.2 Postmarketing Experience

The following hypersensitivity/allergic reactions have been reported in patients treated with BAT:

- Anaphylactic shock
- Angioedema
- Urticaria

6.3 Immunogenicity

As with all therapeutic proteins, there is potential for immunogenicity. All subjects from the two clinical trials were tested for immunogenicity against BAT at baseline and at the end of the studies (Day 28) using a validated assay. Eleven subjects seroconverted during the course of the two trials. One subject from each clinical trial experienced a moderate allergic reaction during the administration of BAT. Both subjects were negative for anti-BAT antibodies at baseline and at the end of their respective studies. The detection of antibody formation is highly dependent on the sensitivity and specificity of the assay. Additionally, the observed incidence of antibody (including neutralizing antibody) positivity in an assay may be influenced by several factors including assay methodology, sample handling, timing of sample collection, concomitant medications, and underlying disease. For these reasons, comparison of the incidence of antibodies to BAT with the incidence of antibodies to other products may be misleading.

7 DRUG INTERACTIONS

Drug Laboratory Interactions: Blood Glucose Testing

BAT contains maltose which can interfere with certain types of blood glucose monitoring systems [see Warnings and Precautions (5.4)]. Only test systems that are glucose-specific should be used in patients receiving BAT. This interference can result in falsely elevated glucose readings that can lead to untreated hypoglycemia or to inappropriate insulin administration, resulting in life-threatening hypoglycemia.

The product information of the blood glucose testing system, including that of the test strips, should be carefully reviewed to determine if the system is appropriate for use with maltose-containing parenteral systems. If any uncertainty exists, contact the manufacturer of the testing system to determine if the system is appropriate for use with maltose-containing parenteral products.

8 USE IN SPECIFIC POPULATIONS

8.1 Pregnancy

Risk Summary

There are no human or animal data to establish the presence or absence of BAT associated risk.

8.2 Lactation

Risk Summary

There are no data to assess the presence or absence of BAT in human milk, the effects on the breastfed child, or the effects on milk production/excretion.

Consider the developmental and health benefits of breastfeeding along with the mother’s clinical need for BAT and any potential adverse effects on the breastfed child from BAT or from the underlying maternal condition.

8.4 Pediatric Use

The effectiveness of BAT has not been established in pediatric patients. Limited pediatric safety data are available.

Fifteen pediatric subjects (age 10 days to 17 years; including 1 newborn, 3 infants and toddlers, 4 children and 7 adolescents) received BAT under the CDC expanded access clinical study. A 3-year old subject and an infant received two infant doses, and 13 pediatric subjects received one pediatric dose according to Salisbury Rule [Table 2].

Two adverse reactions were reported in two pediatric subjects. One subject experienced an adverse reaction of pyrexia following infusion of BAT, while the other subject experienced a serious adverse reaction of hemodynamic instability characterized by tachycardia, bradycardia, and asystole during infusion of BAT.

Dosing in pediatric patients is based on Salisbury Rule.

8.5 Geriatric Use

The safety, pharmacokinetics, and effectiveness of BAT have not been established in geriatric subjects.

Thirty-six geriatric subjects received BAT under the CDC expanded access clinical study. One geriatric subject experienced rash as an adverse reaction following infusion of BAT.

11 DESCRIPTION

BAT [Botulism Antitoxin Heptavalent (A, B, C, D, E, F, G) – (Equine)] is a sterile solution of F(ab’)2 and F(ab') 2-related antibody fragments prepared from plasma obtained from horses that have been immunized with a specific serotype of botulinum toxoid and toxin. To obtain the final heptavalent product, the seven antitoxin serotypes are blended. BAT is supplied in a 50 milliliter vial size, with a fill volume ranging from 10 to 26 milliliters per vial. BAT is administered intravenously.

The manufacturing process for each antitoxin type includes cation-exchange chromatography to purify the immune globulin fraction, digestion with pepsin to produce F(ab')2 plus F(ab')2-related immune globulin fragments, anion exchange chromatography to remove the pepsin as well as other impurities and filtration. In addition, the manufacturing process includes two viral inactivation/removal steps; solvent/detergent (S/D) treatment and virus filtration [Table 4].

The S/D treatment step is effective at inactivating known lipid-enveloped viruses such as equine encephalitis, equine arteritis, West Nile virus, equine infectious anemia, equine herpes virus, rabies, and equine influenza. The BAT manufacturing process also includes a robust filtration step that is effective in reducing the levels of some lipid-enveloped viruses (listed above) as well as non-enveloped viruses including equine rhinovirus, equine adenoviruses and adeno-associated viruses, and equine parvovirus.

Table 4 Viral Clearance Capacity of the BAT Process
 | Enveloped |  |  |  |  | Non-enveloped
Genome | RNA | RNA | RNA | DNA | RNA | DNA | DNA | RNA
Virus | XMuLV | WNV | BVDV | PRV | PI3 | Ad2 | Porcine Parvovirus | EMC
Family | Retro | Flavi | Flavi | Herpes | Paramyxo | Adeno | Parvo | Picorna
Size (nm) | 80-110 | 40-70 | 50-70 | 150-200 | 100-200 | 70-100 | 18-24 | 25-30
First-generation Virus Filter
Virus Filtration (log10) | ≥2.7 | ≥2.1 | ≥4.5 | n.t | n.t. | ≥4.7 | 4.5 | ≥4.5
S/D (log10) | ≥4.3 | ≥5.1 | n.t. | ≥5.1 | ≥5.5 | n.t. | n.t. | n.t.
Total Reduction (log10) | ≥7.0 | ≥7.2 | ≥4.5 | ≥5.1 | ≥5.5 | ≥4.7 | 4.5 | ≥4.5
Second-generation Virus Filter
Virus Filtration (log10) | ≥4.3a | ≥4.3a | n.t. | ≥4.3a | ≥4.3a | ≥4.2 | ≥4.3b | ≥5.0
S/D (log10) | ≥4.3 | ≥5.1 | n.t. | ≥5.1 | ≥5.5 | n.t. | n.t. | n.t.
Total Reduction (log10) | ≥8.6 | ≥9.4 | n.t. | ≥9.4 | ≥9.8 | ≥4.2 | ≥4.3b | ≥5.0
XMuLV: Xenotropic Murine Leukemia Virus; specific model for equine infectious anemia, and a model for lipid-enveloped RNA viruses of similar size, such as vesicular stomatitis virus (Rhabdo family).
WNV: West Nile Virus; relevant virus, and specific model for lipid-enveloped RNA viruses, including the arboviruses, which contains both Flavividae and Togaviridae and includes equine encephalitis viruses (Toga family) and equine viral arteritis (Arteri family, formerly a Toga virus).
BVDV: Bovine Viral Diarrhea Virus; relevant virus, and specific model for lipid-enveloped RNA viruses, including the arboviruses, which contains both Flavividae and Togaviridae and includes equine encephalitis viruses (Toga family) and equine viral arteritis (Arteri family, formerly a Toga virus).
PRV: Pseudorabies Virus; specific model for equine herpes viruses and non-specific model for lipid-enveloped viruses.
PI3: Parainfluenza III Virus; model for lipid enveloped RNA viruses, and viruses of the similar family, orthomyxo, which includes equine influenza virus.
Ad2: Adenovirus; specific model for equine adenovirus.
EMC: Encephalomyocarditis Virus; specific model for equine parvovirus and adeno-associated virus, non-specific model for small lipid and non-lipid enveloped viruses.
n.t. – not tested
a The lowest parvovirus log reduction factor of ≥4.3 is applied based upon the mechanism of removal by size exclusion.
bThe PPV log10 reduction factor was validated using worst-case or varying conditions for applied volume, protein concentrations, and filtration

BAT is formulated with 10% maltose and 0.03% polysorbate 80. The formulated bulk material contains approximately 3-7 g% (30-70 milligrams/milliliter) protein.

The product potency is expressed in units based on the mouse neutralization assay (MNA). Each unit of BAT is designed to neutralize 10,000 mouse intraperitoneal lethal dose 50% units (MIPLD50) of botulinum neurotoxin for serotype A, B, C, D, F, and G and 1,000 MIPLD50 of serotype E.

12 CLINICAL PHARMACOLOGY

12.1 Mechanism of Action

The mechanism of action of BAT is through passive immunization with equine polyclonal antibody fragments (primarily F(ab′)2 and Fab) against botulinum neurotoxin (BoNT) A, B, C, D, E, F, and G. In the circulation the polyclonal antibody fragments bind to free BoNT. This prevents the BoNT from interacting with ganglioside anchorage sites and protein receptors on the cholinergic nerve endings. In turn this prevents BoNT internalization into the target cells. The antibody/antigen complexes are then cleared from the circulation by the organs involved in processing immune complexes.

Experimental evidence concerning the amount of circulating antitoxin needed to counteract BoNT intoxication is not fully documented. The outcome of treatment depends, as it does with other comparable conditions, largely on the time interval elapsing after the onset of symptoms and antitoxin administration.

12.2 Pharmacodynamics

A proof-of-concept clinical dose-response trial was conducted using the extensor digitorum brevis (EDB) muscle of the foot as a model for measuring muscle paralysis after exposure to botulism toxin. In this model, BAT prevented subjects from experiencing a decrease in muscle function after exposure to botulinum neurotoxin (BoNT) serotypes A and B. Subjects treated with placebo (n=10) demonstrated a loss of greater than 50% EDB muscle function within 3 days of exposure to BoNT serotypes A and B. In the BAT arm of the trial (n=16), EDB muscle function was stable over time indicating that BAT was effective in preserving muscle function for up to 28 days following exposure to both BoNT serotype A and B.

12.3 Pharmacokinetics

The pharmacokinetics (PK) of the seven botulism antitoxin serotypes was determined in healthy human subjects following IV administration of either one (n=20) or two vials (n=20) of BAT. The various PK parameters are summarized in Table 5.

The PK parameters varied based upon the antitoxin serotype measured. Antitoxin serotypes D and E had the shortest half-lives. While antitoxin serotype B and C had the longest half-lives. The AUC0-∞ and Cmax values increased in a dose proportional fashion as the BAT dose increased from one to two vials. In addition, mean clearance values appeared to be similar between both treatment groups for the seven antitoxin serotypes, suggesting dose linearity of BAT over the dose range studied.

Table 5 Pharmacokinetic Parameters (Mean) for Antitoxin Serotypes A Through G in Humans Following Intravenous Administration of either One or Two Vials of BAT
Antitoxin Serotype | Treatment Group | AUC0-∞ (U*hr/mL) | Cmax (U/mL) | t1/2 (hr) | Cl (mL/hr) | Vd (mL)
A | 1 Vial | 26.00 | 2.69 | 8.64 | 293 | 3637
A | 2 Vials | 56.09 | 6.23 | 10.20 | 285 | 3993
B | 1 Vial | 29.30 | 1.90 | 34.20 | 196 | 9607
B | 2 Vials | 62.55 | 4.28 | 57.10 | 181 | 14865
C | 1 Vial | 37.34 | 2.26 | 29.60 | 144 | 6066
C | 2 Vials | 86.25 | 4.89 | 45.60 | 127 | 8486
D | 1 Vial | 7.62 | 0.81 | 7.51 | 137 | 1465
D | 2 Vials | 14.83 | 1.60 | 7.77 | 151 | 1653
E | 1 Vial | 7.16 | 0.94 | 7.75 | 1250 | 14172
E | 2 Vials | 15.66 | 1.75 | 7.32 | 1110 | 11596
F | 1 Vial | 31.40 | 2.37 | 14.10 | 169 | 3413
F | 2 Vials | 63.19 | 4.29 | 18.20 | 168 | 4334
G | 1 Vial | 7.05 | 0.59 | 11.70 | 149 | 2372
G | 2 Vials | 14.66 | 1.19 | 14.70 | 144 | 3063
AUC = Area Under the Concentration Curve; Cl = Clearance; Cmax = Maximum Serum Concentration; BAT = Botulism Antitoxin Heptavalent (A, B, C, D, E, F, G) – (Equine); t1/2 = Half-life; Tmax = Time to Maximum Serum Concentration; U = Unit; Vd = Volume of Distribution.

13 NONCLINICAL TOXICOLOGY

13.2 Animal Toxicology and Pharmacology

Toxicological studies were not conducted for BAT or its components.

The evaluation of new treatment options for botulism using controlled human trials is unethical and infeasible. Therefore the effectiveness of BAT for treatment of botulism is based on well controlled efficacy studies conducted in guinea pigs and rhesus macaques.

Guinea Pig

In a controlled therapeutic efficacy study, guinea pigs were intoxicated with various BoNT serotypes (A, B, C, D, E, F or G) at a dose of 1.5x guinea pig intramuscular lethal dose 50% units (GPIMLD50) via intramuscular injection into the right hind limb. The animals were then treated with either placebo control or 1x scaled human dose of BAT (weight/weight based on an average human body weight of 70 kilograms), after the onset of moderate clinical signs of botulism (right hind limb weakness, salivation, lacrimation, weak limbs and noticeable changes in breathing rate or pattern). Treatment with BAT resulted in a statistically significant improvement in the survival rate of animals across all of the serotypes tested [Table 6].

Table 6 Summary of Guinea Pig Survival Data from BAT Therapeutic Efficacy Study
Neurotoxin Serotype | Treatment Group | Survival Rate (%) | Two-sided Fisher’s Exact Test (p-value)
A | 1x BAT | 34/34 (100%) | p<0.0001
A | Placebo Control | 0/34 (0%) | p<0.0001
B | 1x BAT | 34/34 (100%) | p<0.0001
B | Placebo Control | 1/34 (3%) | p<0.0001
C | 1x BAT | 33/34 (97%) | p<0.0001
C | Placebo Control | 4/34 (12%) | p<0.0001
D | 1x BAT | 33/34 (97%) | p<0.0001
D | Placebo Control | 5/34 (15%) | p<0.0001
E | 1x BAT | 34/34 (100%) | p<0.0001
E | Placebo Control | 0/34 (0%) | p<0.0001
F | 1x BAT | 34/34 (100%) | p<0.0001
F | Placebo Control | 4/34 (12%) | p<0.0001
G | 1x BAT | 34/34 (100%) | p<0.0001
G | Placebo Control | 17/34 (50%) | p<0.0001
BAT = Botulism Antitoxin Heptavalent (A, B, C, D, E, F, G) – (Equine).

Nonhuman Primate

In a controlled therapeutic efficacy study, rhesus macaques were intoxicated with BoNT serotype A delivered intravenously at a dose of 1.7x nonhuman primate intravenous lethal dose 50% (NHPLD50) units per kilogram of body weight. The animals were then treated with either placebo control or 1x scaled human dose of BAT (weight/weight based on an average human body weight of 70 kilograms), after the onset of clinical signs of botulism (ptosis, muscular weakness, or respiratory distress). Treatment with BAT resulted in a statistically significant improvement in the survival rate [Table 7].

Table 7 Summary of Rhesus macaque Survival Data from BAT Therapeutic Efficacy Study
Treatment Group | Survival Rate (%) | Two-sided Fisher’s Exact Test (p-value)
1x BAT | 14/30 (47%) | p<0.0001
Placebo Control | 0/30 (0%) | p<0.0001
BAT = Botulism Antitoxin Heptavalent (A, B, C, D, E, F, G) – (Equine).

14 CLINICAL STUDIES

The effectiveness of BAT is based on efficacy studies demonstrating a survival benefit in animal models of botulism [see Nonclinical Toxicology (13.2)]. The safety has been tested in healthy adults and patients with suspected botulism who were treated with BAT under an expanded access clinical study.

The pharmacokinetic, pharmacodynamic, and safety profiles of BAT have been evaluated in two clinical studies. In these clinical studies, BAT was shown to have an acceptable safety profile when one or two vials of BAT were administered intravenously to healthy subjects.

In a randomized, single-center, double-blind trial the pharmacokinetics and safety of BAT was evaluated in 40 healthy subjects receiving either one (n = 20) or two (n = 20) vials of BAT by IV infusion. Serum BAT levels were measured in the subjects using the Mouse Neutralization Assay (MNA) [see Clinical Pharmacology (12.3)].

In a randomized single center, double-blind trial the pharmacodynamics and safety of BAT was evaluated in 26 healthy subjects receiving either a single vial of BAT (n=16) or placebo (n=10) by IV infusion. The effects of BAT in preventing paralysis of the EDB foot muscle following administration of botulinum neurotoxin serotype A or B was determined [see Clinical Pharmacology (12.2)].

To provide additional support for the efficacy demonstrated in the animal models, a preliminary analysis of data from a Centers for Disease Control and Prevention (CDC) open-label, observational expanded access clinical study for the treatment of subjects with suspected or confirmed botulism with BAT was conducted. Across the 148 subjects treated with BAT in the period analyzed, 109 subjects had a final discharge diagnosis of suspected or confirmed botulism and were included in the analysis population. The median time from the onset of botulism symptoms to treatment with BAT was 3.6 days (range: 0.25 – 38 days). Early treatment (≤ 2 days after onset of symptoms) with BAT was associated with a shorter length of hospitalization, duration in intensive care unit (ICU) and duration of mechanical ventilation compared to later treatment [Table 8] and is consistent with the mechanism of action [see Clinical Pharmacology (12.1)].

Table 8 Summary of Duration of Hospitalization, ICU Stay and Mechanical Ventilation for CDC Patients Treated with BAT
 | Time from Symptoms to Treatment | Number of Patients; (N) | Mean Duration in Days (SD)
Hospitalization | ≤ 2 Days | 14 | 12.4 (9.28)
Hospitalization | > 2 Days | 72 | 26.1 (26.37)
ICU Stay | ≤ 2 Days | 13 | 9.2 (7.40)
ICU Stay | > 2 Days | 70 | 15.8 (18.76)
Mechanical Ventilation | ≤ 2 Days | 9 | 11.6 (7.83)
Mechanical Ventilation | > 2 Days | 41 | 23.4 (21.11)

15 REFERENCES

1. Lack JA, Stuart-Taylor ME. Calculation of drug dosage and body surface area of children. Br J Anaesth. 1997; 78:601-605.

16 HOW SUPPLIED/STORAGE AND HANDLING

16.1 How Supplied

BAT is supplied in 50 milliliter glass vials seated with a rubber stopper and a plastic cap, with a fill volume ranging from 10 to 26 milliliters per vial. Each vial, regardless of size or fill volume contains a minimum potency of > 4,500 U serotype A antitoxin, > 3,300 U serotype B antitoxin, > 3000 U serotype C antitoxin, > 600 U serotype D antitoxin, > 5,100 U serotype E antitoxin, > 3,000 U serotype F antitoxin, and > 600 U serotype G antitoxin.

BAT is not made with natural rubber latex.

NDC Number Product Description

60492-0075-1 A 50 milliliter single dose vial

60492-0075-2 Six 50 milliliter single dose vials in a shelf carton.

60492-0075-4 A 50 milliliter single dose vial in a unit carton.

16.2 Storage and Handling

- Store frozen at or below 5°F (≤ -15°C) until used.
- Once thawed, Botulism Antitoxin Heptavalent (A, B, C, D, E, F, G) – (Equine) may be stored at 2-8°C (36-46°F) for a maximum of 36 months or until 48 months from the date of manufacture, whichever comes first. Do not refreeze.
- Once punctured, use the vial contents to prepare the infusion bag and administer as soon as possible.
- BAT vials are for single use only and contain no preservative. Discard any unused portion.

17 PATIENT COUNSELING INFORMATION

See FDA-approved patient labeling (Patient Information).

- Inform patients of the following:
  - BAT is prepared from equine plasma and may contain infectious agents such as viruses that can cause disease.
  - The risk that such products will transmit an infectious agent has been reduced by screening the horses for prior exposure to certain viruses, by testing for the presence of certain current viral infections, and by inactivating and/or removing certain viruses during manufacturing.
  - Despite these measures, such products can still potentially transmit disease.
  - There is also the possibility that unknown infectious agents may be present in such products.
- Inform patients that persons who have received previous therapy with an equine-derived antivenom/antitoxin, have known allergies to horses, have asthma or get hay fever (seasonal allergies) may be at increased risk of hypersensitivity reactions and should only receive BAT if the benefits outweigh the risks.
- Advise patients about the potential interference with non-glucose specific monitoring systems.
  - The maltose contained in BAT can interfere with some types of blood glucose monitoring systems.
  - Only testing systems that are glucose-specific should be used in patients receiving BAT.
  - This interference can result in falsely elevated glucose readings that can lead to untreated hypoglycemia or to inappropriate insulin administration, resulting in life-threatening hypoglycemia.

BAT® and any and all Emergent BioSolutions Inc. brand, product, service and feature names, logos and slogans are trademarks or registered trademarks of Emergent BioSolutions Inc. or its subsidiaries in the United States or other countries. All rights reserved.

Manufactured by:

Emergent BioSolutions Canada Inc.
155 Innovation Drive
Winnipeg, Manitoba
Canada, R3T 5Y3

U.S. License No. 2084

PATIENT INFORMATION

BAT® [Botulism Antitoxin Heptavalent (A, B, C, D, E, F, G) – (Equine)]

What is botulism?

Botulism is a muscle-paralyzing disease caused by a toxin made by a bacterium called Clostridium botulinum.

Botulism can cause the following conditions:

- Double vision,
- Blurred vision,
- Drooping eyelids,
- Slurred speech,
- Difficulty swallowing,
- Dry mouth,
- Muscle weakness that spreads through the body,
- Difficulty breathing.

Botulism can also cause paralysis and death. After a person is exposed to the toxin, problems can start as early as three hours or as late as a few days. It can take weeks or months to get better. During that time, many people need special care in the hospital.

The effectiveness of BAT has been studied in animals with botulism.

What is BAT?

BAT is a botulism antitoxin made from the plasma of horses. It contains antibody fragments which can neutralize botulism toxins. BAT may make the illness from botulism less severe. Treatment with BAT will not reverse the paralysis, but may decrease the duration and extent of paralysis.

Who should use BAT?

Your doctor may give you BAT if they suspect that you have been exposed to botulism toxin. You should get the treatment as quickly as possible to stop the progression of the illness.

Unless the benefits outweigh the risks, you should not receive BAT if you have a known history of allergies to horses or horse blood products, asthma or hay fever (seasonal allergies).

How will you receive BAT?

BAT is given as an injection into your vein. Your doctor will determine the dose of BAT. The treatment may take several hours to administer. Your doctor will decide if you need more than one injection.

What are the possible or reasonably likely side effects of BAT?

The most common side effects of BAT are:

- Headache
- Fever
- Rash
- Hives
- Chills
- Nausea
- Swelling

Some people have a chilly feeling, difficulty breathing, and have a quick rise in body temperature within the first 20 to 60 minutes after getting BAT. This can be managed by your doctor.

BAT can cause allergic reactions. Tell your doctor or go to the emergency department right away if you have trouble breathing, swelling of your tongue or lips, or a very fast heart rate because this can be signs of a serious allergic reaction.

Tell your doctor if you get pains in your joints and back, fever, and a rash within one to three weeks after getting BAT. These can be signs of “serum sickness” and can last for a few weeks. Your doctor can give you medicine to help with serum sickness.

Talk to your doctor about any side effects that concern you. You can ask your doctor for additional prescribing information that is available to healthcare professionals.

What other information do you need to know about BAT?

BAT is made from horse plasma. The horses are carefully screened and the plasma is carefully cleaned, but there is a small risk that it may give you a virus. Talk to your doctor if you have any symptoms that concern you.

You may report side effects directly to Emergent BioSolutions Canada Inc. at 1-800-768-2304 or to the FDA’s MedWatch reporting system at 1-800-FDA-1088.

BAT® and any and all Emergent BioSolutions Inc. brand, product, service and feature names, logos and slogans are trademarks or registered trademarks of Emergent BioSolutions Inc. or its subsidiaries in the United States or other countries. All rights reserved.

Manufactured By:

Emergent BioSolutions Canada Inc.
155 Innovation Drive
Winnipeg, Manitoba
Canada, R3T 5Y3

US License No. 2084